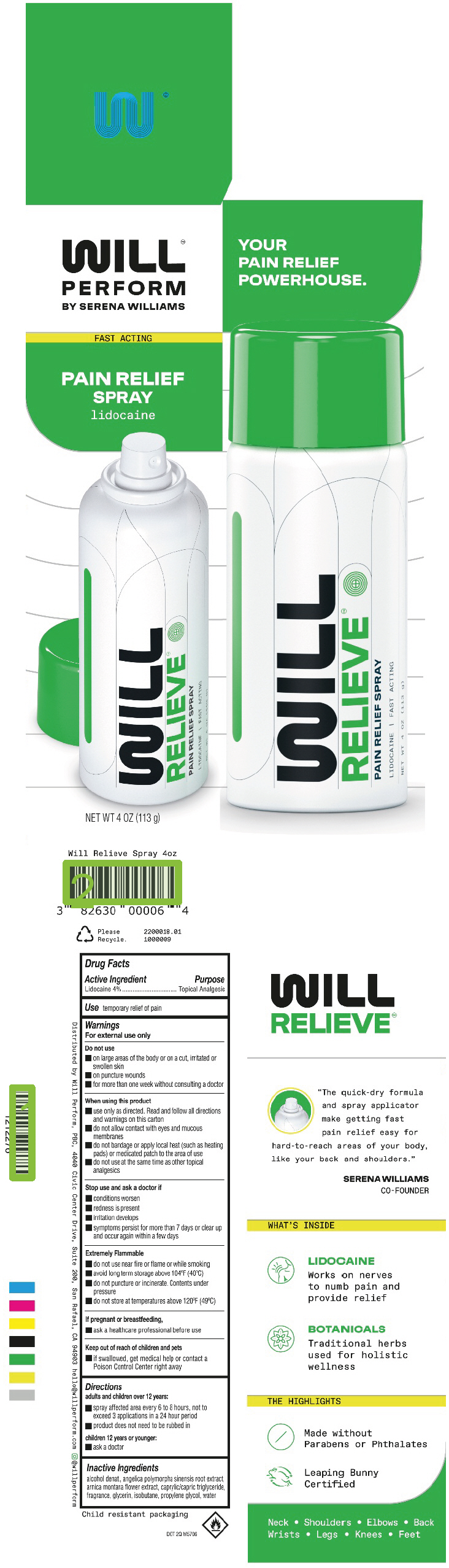 DRUG LABEL: Will Relieve
NDC: 82630-003 | Form: AEROSOL, SPRAY
Manufacturer: Will Perform, PBC
Category: otc | Type: HUMAN OTC DRUG LABEL
Date: 20231006

ACTIVE INGREDIENTS: Lidocaine 4.52 g/113 g
INACTIVE INGREDIENTS: Propylene Glycol; Medium-Chain Triglycerides; ANGELICA SINENSIS ROOT; Glycerin; Arnica Montana Flower; Isobutane; Alcohol

Will Relieve™ Spray

Drug Facts

Active Ingredient

Lidocaine 4%

Purpose

Topical Analgesic

Use

temporary relief of pain

Warnings

For external use only

Do not use

- on large areas of the body or on a cut, irritated or swollen skin
- on puncture wounds
- for more than one week without consulting a doctor

When using this product

- use only as directed. Read and follow all directions and warnings on this carton
- do not allow contact with eyes and mucous membranes
- do not bandage or apply local heat (such as heating pads) or medicated patch to the area of use
- do not use at the same time as other topical analgesics

Stop use and ask a doctor if

- conditions worsen
- redness is present
- irritation develops
- symptoms persist for more than 7 days or clear up and occur again within a few days

Extremely Flammable

- do not use near fire or flame or while smoking
- avoid long term storage above 104°F (40°C)
- do not puncture or incinerate. Contents under pressure
- do not store at temperatures above 120°F (49°C)

PREGNANCY OR BREAST FEEDING

If pregnant or breastfeeding,

- ask a healthcare professional before use

Keep out of reach of children and pets

- if swallowed, get medical help or contact a Poison Control Center right away

Directions

adults and children over 12 years:

- spray affected area every 6 to 8 hours, not to exceed 3 applications in a 24 hour period
- product does not need to be rubbed in

children 12 years or younger:

- ask a doctor

Inactive Ingredients

alcohol denat., angelica polymorpha sinensis root extract, arnica montana flower extract, caprylic/capric triglyceride, fragrance, glycerin, isobutane, propylene glycol, water

Distributed by Will Perform, PBC, 4040 Civic Center Drive, Suite 200, San Rafael, CA 94903

PRINCIPAL DISPLAY PANEL - 113 g Can Carton

WILL™
PERFORM
BY SERENA WILLIAMS

FAST ACTING

PAIN RELIEF
SPRAY
lidocaine

NET WT 4 OZ (113 g)